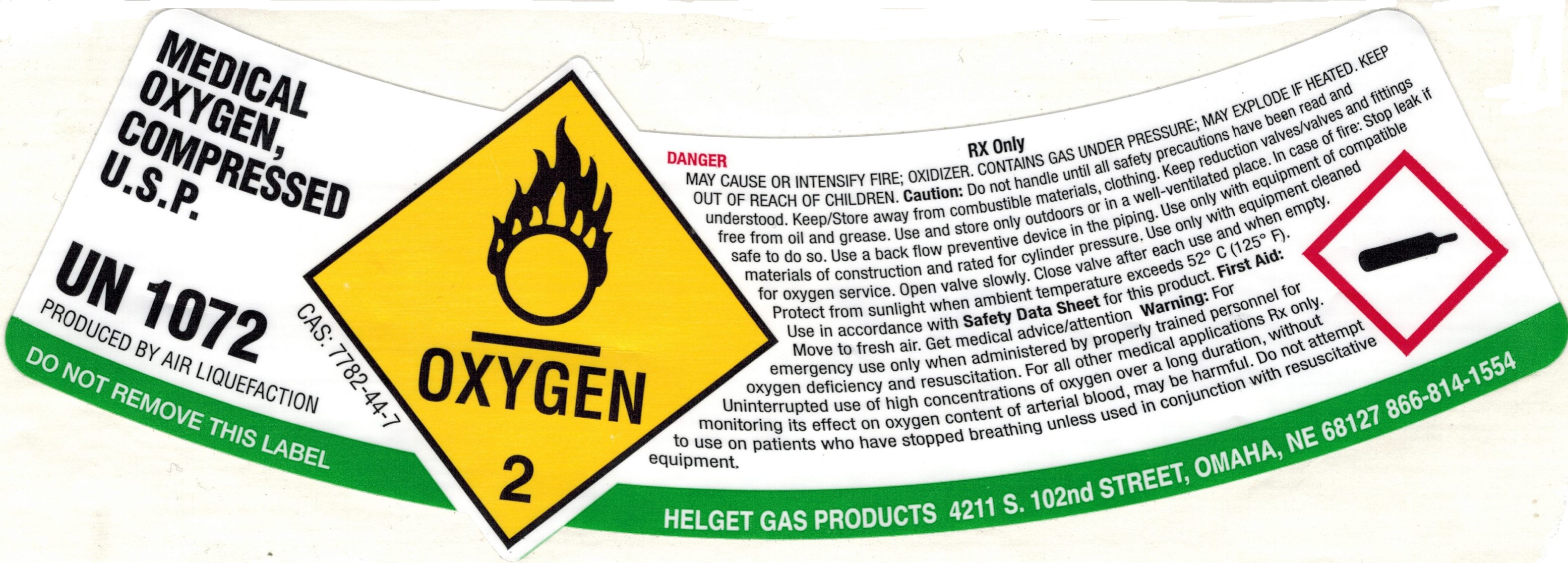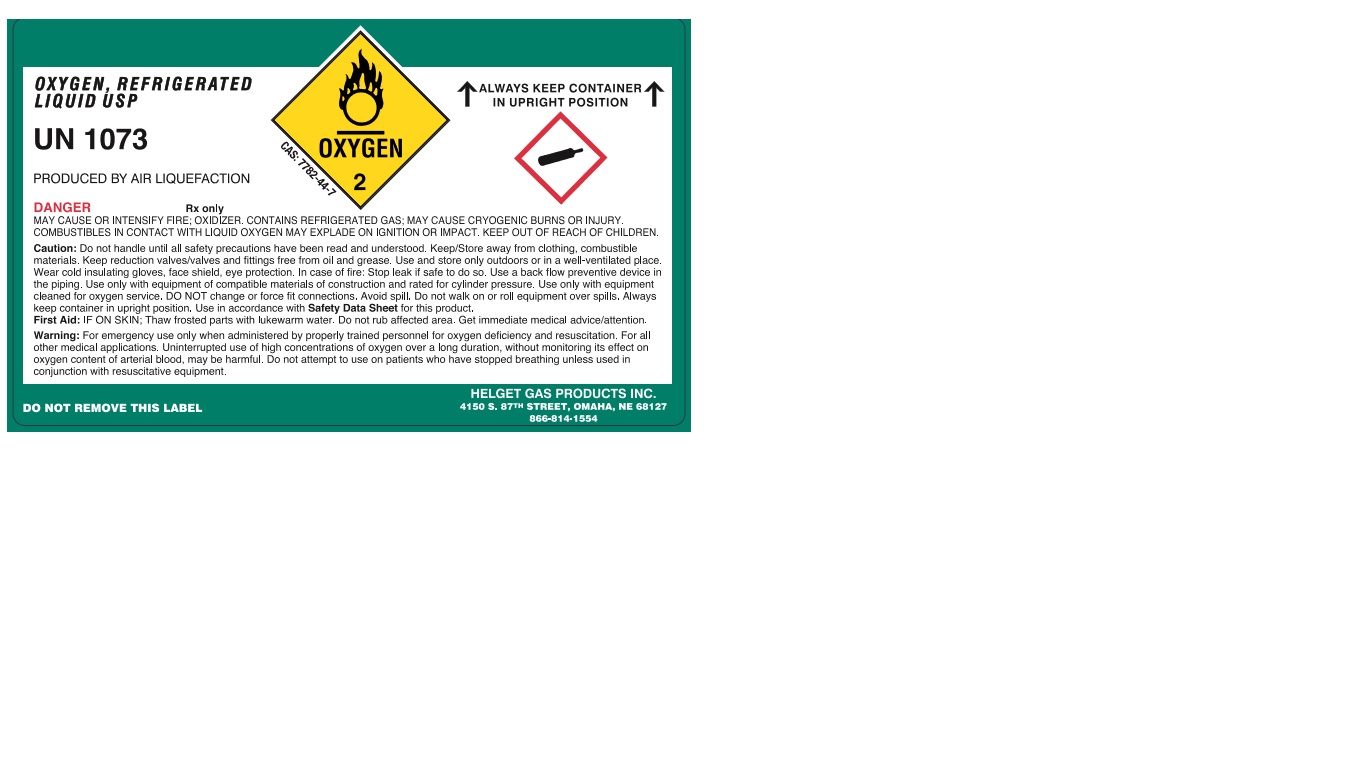 DRUG LABEL: Oxygen
NDC: 52086-004 | Form: GAS
Manufacturer: Helget Gas Products
Category: prescription | Type: HUMAN PRESCRIPTION DRUG LABEL
Date: 20220208

ACTIVE INGREDIENTS: OXYGEN 999 mL/1 L

Oxygen

PACKAGE LABEL

OXYGEN, REFRIGERATED LIQUID USP
UN1073
PRODUCED BY AIR LIQUEFACTION
ALWAYS KEEP CONTAINER IN UPRIGHT POSITION
CAS:7782-44-7
DANGER
MAY CAUSE OR INTENSIFY FIRE; OXIDIZER. CONTAINS REFRIGERATED GAS; MAY CAUSE CRYOGENIC BURNS OR INJURY. COMBUSITBLES IN CONTACT WITH LIQUID OXYGEN MAY EXPLADE ON IGNITION OR IMPACT. KEEP OUT OF REACH OF CHILDREN.
Caution: Do not handle until all safety precautions have been read and understood. Keep/Store away from clothing, combustible materials. Keep reduction valves/valves and fittings free from oil and grease. Use and store only outdoors or in a well-ventilated place. Wear cold insulating gloves, face shield, eye protection. In case of fire: Stop leak if safe to do so. Use a back flow preventive device in the piping. Use only with equipment of compatible materials of construction and rated for cylinder pressure. Use only with equipment cleaned for oxygen service. DO NOT change or force fit connections. Avoid spill. Do not walk on or roll equipment over spills. Always keep container in upright position. Use in accordance with Safety Data Sheet for this product.
First Aid: IF ON SKIN; Thaw frosted parts with lukewarm water. Do not rub affected area. Get immediate medical advice/attention.
Warning: For emergency use only when administered by properly trained personnel for oxygen deficiency and resuscitation. For all other medical applications. Uninterrupted use of high concentrations of oxygen over a long duration, without monitoring its effect on oxygen content of arterial blood, may be harmful. Do not attempt to use on patients who have stopped breathing unless used in conjunction with resuscitative equipment.
DO NOT REMOVE THIS LABEL
HELGET GAS PRODUCTS INC.
4150 S. 87TH STREET, OMAHA, NE 68127
866-814-1554

PACKAGE LABEL

MEDICAL OXYGEN, COMPRESSED U.S.P.
UN1072
PRODUCED BY AIR LIQUEFACTION
DO NOT REMOVE THIS LABEL
RX Only
DANGER
MAY CAUSE OR INTESIFY FIRE; OXIDIZER. CONTAINS GAS UNDER PRESSURE; MAY EXPLODE IF HEATED. KEEP OUT OF REACH OF CHILDREN. Caution: Do not handle until all safety precautions have been read and understood. Keep/Store away from combustible materials, clothing. Keep reduction valves/valves and fittings free from oil and grease. Use and store only outdoors or in a well-ventilated place. In case of fire: Stop leak if materials of construction and rated for cylinder pressure. Use only with equipment cleaned for oxygen service. Open valve slowly. Close valve after each use and when empty. Protect from sunlight when ambient temperature exceeds 52 C (125F). Use in accordance with Safety Data Sheet for this product. First Aid: Move to fresh air. Get medical advice/attention. Warning: For emergency use only when administered by properly trained personnel for oxygen deficiency and resuscitation. For all other medical applications Rx only. Uninterrupted use of high concentrations of oxygen over a long duration, without monitoring its effect on oxygen content of arterial blood, may be harmful. Do not attempt to use on patients who have stopped breathing unless used in conjunction with resuscitative equipment.
HELGET GAS PRODUCTS 4211 S. 102nd STREET, OMAHA, NE 68127 866-814-1554